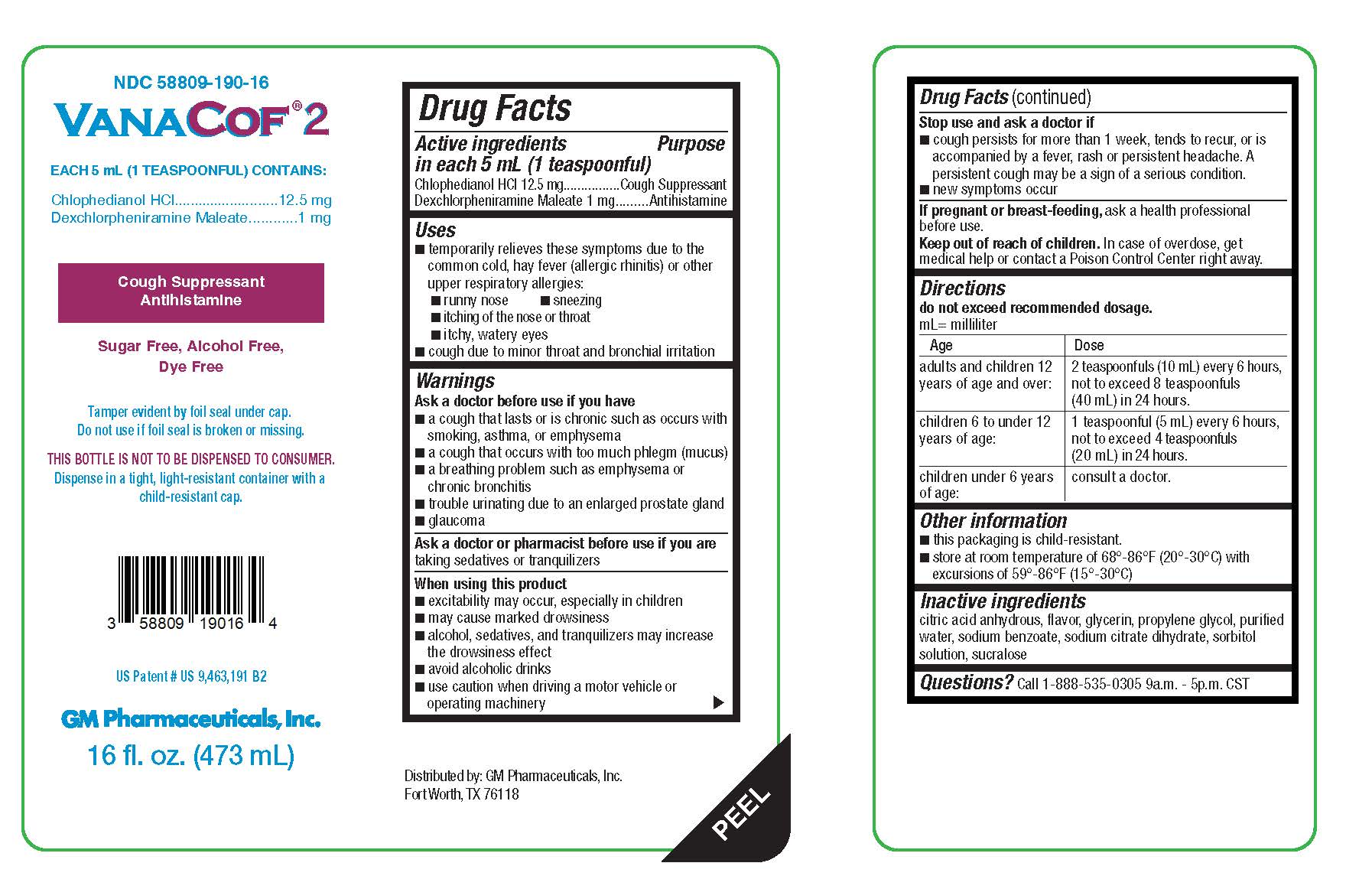 DRUG LABEL: VanaCof 2
NDC: 58809-190 | Form: SOLUTION
Manufacturer: GM Pharmaceuticals, INC
Category: otc | Type: HUMAN OTC DRUG LABEL
Date: 20260108

ACTIVE INGREDIENTS: DEXCHLORPHENIRAMINE MALEATE 1 mg/5 mL; CHLOPHEDIANOL HYDROCHLORIDE 12.5 mg/5 mL
INACTIVE INGREDIENTS: WATER; PROPYLENE GLYCOL; SODIUM BENZOATE; SORBITOL SOLUTION; ANHYDROUS CITRIC ACID; SUCRALOSE; GLYCERIN; TRISODIUM CITRATE DIHYDRATE

VanaCof® 2

Active ingredients in each 5 mL (1 teaspoonful)

Chlophedianol HCI 12.5 mg

Dexchlorpheniramine Maleate 1 mg

Purpose

Cough Suppressant

Antihistamine

Uses

■ temporarily relieves these symptoms due to the common cold, hay fever (allergic rhinitis) or other upper respiratory allergies:

■ runny nose

■ sneezing

■ itching of the nose or throat

■ itchy, watery eyes

■ cough due to minor throat and bronchial irritation

Warnings

Ask a doctor before use if you have

■ a cough that lasts or is chronic such as occurs with smoking, asthma, or emphysema

■ a cough that occurs with too much phlegm (mucus)

■ a breathing problem such as emphysema or chronic bronchitis

■ trouble urinating due to an enlarged prostate gland

■ glaucoma

Ask a doctor or pharmacist before use if you are

taking sedatives or tranquilizers

When using this product

■ excitability may occur, especially in children

■ may cause marked drowsiness

■ alcohol, sedatives, and tranquilizers may increase the drowsiness effect

■ avoid alcoholic drinks

■ use caution when driving a motor vehicle or operating machinery

Stop use and ask a doctor if

■ cough persists for more than 1 week, tends to recur, or is accompanied by a fever, rash or persistent headache. A persistent cough may be a sign of a serious condition.

■ new symptoms occur

If pregnant or breast-feeding,

ask a health professional before use.

Keep out of reach of children.

In case of overdose, get medical help or contact a Poison Control Center right away.

Directions

do not exceed recommended dosage.

adults and children 12 years of age and over: | 2 teaspoonfuls (10 mL) every 6 hours, not to exceed 8 teaspoonfuls (40 mL) in 24 hours.
children 6 to under 12 years of age: | 1 teaspoonful (5 mL) every 6 hours, not to exceed 4 teaspoonfuls (20 mL) in 24 hours.
children under 6 years of age: | consult a doctor.

Other information

■ this packaging is child-resistant.

■ store at room temperature of 68°-86°F (20°-30°C) with excursions of 59°-86°F (15°-30°C)

Inactive ingredients

citric acid anhydrous, flavor, glycerin, propylene glycol, purified water, sodium benzoate, sodium citrate dihydrate, sorbitol solution, sucralose

Questions?

Call 1-888-535-0305 9a.m. - 5p.m. CST

Distributed by: GM Pharmaceuticals, Inc. Fort Worth, TX 76118

PACKAGE LABEL

NDC 58809-190-16

VanaCof® 2

EACH 5 mL (1 TEASPOONFUL) CONTAINS:

Chlophedianol HCI..........................12.5 mg

Dexchlorpheniramine Maleate............1 mg

Cough Suppressant

Antihistamine

Sugar Free, Alcohol Free, Dye Free

Tamper evident by foil seal under cap. Do not use if foil seal is broken or missing.

THIS BOTTLE IS NOT TO BE DISPENSED TO CONSUMER.

Dispense in a tight, light-resistant container with a child-resistant cap.

US Patent # 9,463,191

US Patent # 9,050,289

GM Pharmaceuticals, Inc.

16 fl. oz. (473 mL)